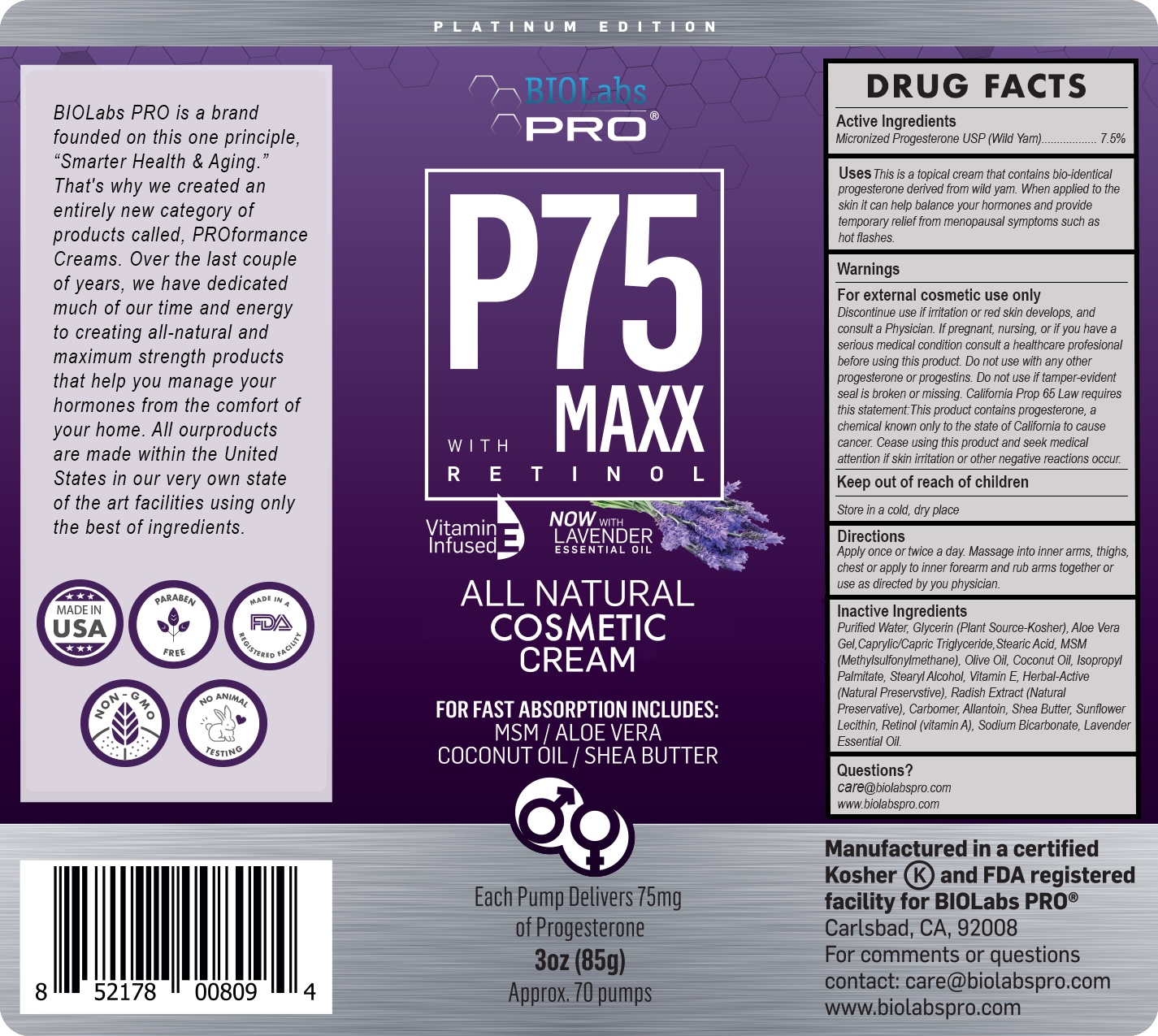 DRUG LABEL: P75 Lav Progesterone Cream
NDC: 82018-0014 | Form: CREAM
Manufacturer: SHYNE BRANDS
Category: otc | Type: HUMAN OTC DRUG LABEL
Date: 20250601

ACTIVE INGREDIENTS: PROGESTERONE 1 mg/1 mg
INACTIVE INGREDIENTS: COCONUT OIL 1 mg/1 mg; SODIUM BICARBONATE 1 mg/1 mg; SHEA BUTTER 1 mg/1 mg; ISOPROPYL PALMITATE 1 mg/1 mg; STEARIC ACID 1 mg/1 mg; GLYCERIN 1 mg/1 mg; LECITHIN, SUNFLOWER 1 mg/1 mg; ALLANTOIN 1 mg/1 mg; ALOE VERA LEAF 1 mg/1 mg; OLIVE OIL 1 mg/1 mg

P75 Lav Progesterone Cream

DRUG FACTS

Active Ingredients

Micronizrd Progesterone USP (Wild Yam) 7.5%

PURPOSE

This is a topical cream that contains bio-identical progesterone derived from wild yam. When applied to the skin it can help balance your hormones and provide temporary relief from menopausal symptoms such as hot flashes.

INDICATIONS AND USAGE

DIRECTIONS: Apply once or twice a day. Massage into inner arms, thighs, chest or apply to inner forearm and rub arms together or use as directed by your Physician.

THIS CONTAINER Yields approximately 70 full pumps or 75 mg of bio-identical Progesterone USP (7.5%) per pump. It also contains Retinol, Vitamin E, Coconut Oil, Shea Butter, and other ingredients to support transdermal bioavailability and overall skin tone. This is an All Natural product. Application is intended for external cosmetic use.

WARNINGS

WARNING: FOR EXTERNAL COSMETIC USE ONLY. Discontinue use if irritation or red skin develops, and consult a Physician. If pregnant, nursing, or if you have a serious medical condition consult a healthcare professional before using this product. Do not use with any other progesterone or progestins. Do not use if tamper-evident seal is broken or missing. California Prop 65 Law requires this statement: This product contains progesterone, a chemical known only to the State of California to cause cancer. Cease using this product and seek medical attention if skin irritation or other negative reactions occur. KEEP OUT OF REACH OF CHILDREN.

PREGNANCY OR BREAST FEEDING

If pregnant or nursing or if you have a serious medical condition consult a healthcare professional before using this product.

Keep Out of Reach of Children.

DOSAGE AND ADMINISTRATION

Apply once or twice a day. Massage into inner arms, thighs, chest or apply to inner forearm and rub arms together or use as directed by you physician.

INACTIVE INGREDIENT

Purified Water Glycerin (Plant source - kosher) Aloe Vera Gel Caprylic/Capric Triglyceride Stearic Acid MSM (Methylsulfonylmethane) Olive Oil Coconut Oil Isopropyl Palmitate Stearyl Alcohol Vitamin E Blend of Essential oils and herbs (Natural Preservative) Radish Extract (Natural Preservative) Carbomer Allantoin Shea Butter Sunflower Lecithin Retinol (vitamin A) Sodium Bicarbonate Lavender Essential Oil

Questions?

care@biolabspro.com

www.biolabspro.com